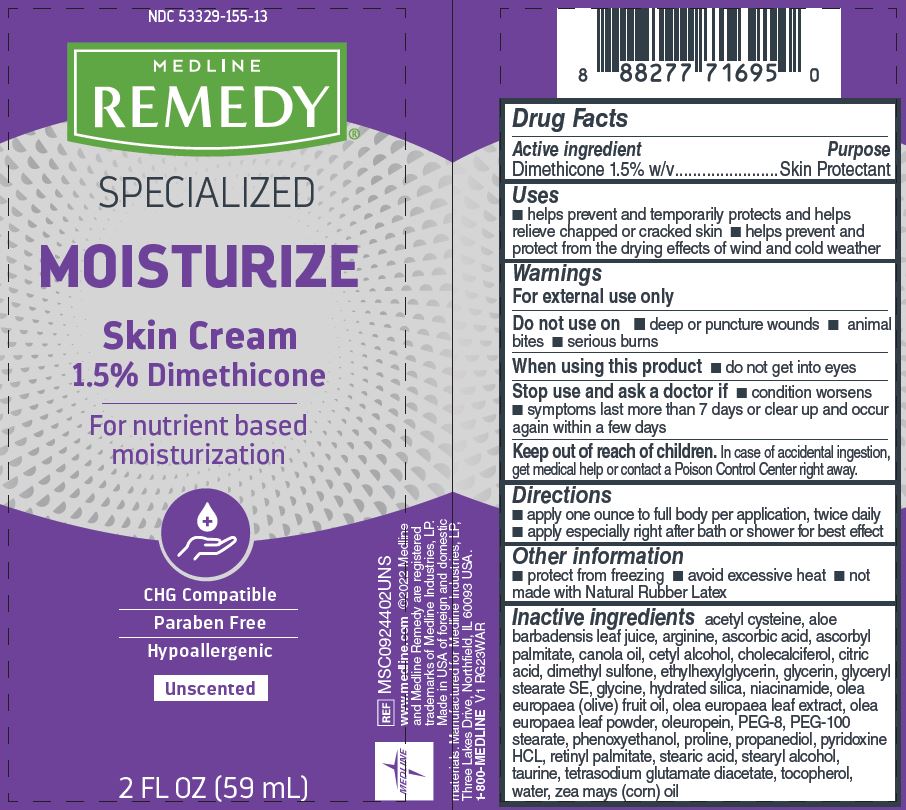 DRUG LABEL: Medline
NDC: 53329-155 | Form: CREAM
Manufacturer: Medline Industries, LP
Category: otc | Type: HUMAN OTC DRUG LABEL
Date: 20251028

ACTIVE INGREDIENTS: DIMETHICONE 15 mg/1 mL
INACTIVE INGREDIENTS: OLIVE OIL; NIACINAMIDE; TETRASODIUM GLUTAMATE DIACETATE; ASCORBIC ACID; PYRIDOXINE HYDROCHLORIDE; WATER; STEARYL ALCOHOL; CORN OIL; .ALPHA.-TOCOPHEROL, DL-; GLYCERIN; STEARIC ACID; VITAMIN A PALMITATE; OLEUROPEIN; HYDRATED SILICA; CANOLA OIL; CETYL ALCOHOL; CHOLECALCIFEROL; PHENOXYETHANOL; PEG-100 STEARATE; POLYETHYLENE GLYCOL 400; ASCORBYL PALMITATE; DIMETHYL SULFONE; PROPANEDIOL; ALOE VERA LEAF; ACETYLCYSTEINE; TAURINE; PROLINE; ARGININE; GLYCERYL STEARATE SE; ANHYDROUS CITRIC ACID; ETHYLHEXYLGLYCERIN; GLYCINE

155 Remedy Specialized Skin Cream

Active ingredient

Dimethicone 1.5% w/v

Purpose

Skin protectant

Uses

- helps prevent and temporarily protects and helps relieve chapped or cracked skin
- helps prevent and protect from the drying effects of wind and cold weather

Warnings

For external use only

Do not use

- deep or puncture wounds
- animal bites
- serious burns

When using this product

- do not get into eyes

Stop use and ask a doctor if

- condition worsens
- symptoms last more than 7 days or clear up and occur again within a few days

Keep out of reach of children.

In case of accidental ingestion, get medical help or contact a Poison Control Center right away.

Directions

- apply one ounce to full body per application, twice daily
- apply especially right after bath or shower for best effect

Other information

- protect from freezing
- avoid excessive heat
- not made with Natural Rubber Latex

Inactive ingredients

acetyl cysteine, aloe barbadensis leaf juice, arginine, ascorbic acid, ascorbyl palmitate, canola oil, cetyl alcohol, cholecalciferol, citric acid, dimethyl sulfone, ethylhexylglycerin, glycerin, glyceryl stearate SE, glycine, hydrated silica, niacinamide, olea europaea (olive) fruit oil, olea europaea leaf extract, olea europaea leaf powder, oleuropein, PEG-8, PEG-100 stearate, phenoxyethanol, proline, propanediol, pyridoxine HCL, retinyl palmitate, stearic acid, stearyl alcohol, taurine, tetrasodium glutamate diacetate, tocopherol, water, zea mays (corn) oil

Manufacturing Information

www.medline.com

©2022 Medline and Medline Remedy

are registered trademarks of

Medline Industries, LP.

Made in USA of foreign

and domestic materials

Manufactured for Medline Industries, LP

Three Lakes Drive, Northfield, IL 60093 USA

1-800-MEDLINE

REF: MSC0924402UNS